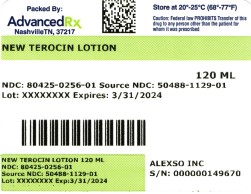 DRUG LABEL: New Terocin
NDC: 80425-0256 | Form: LOTION
Manufacturer: Advanced Rx Pharmacy of Tennessee, LLC
Category: otc | Type: HUMAN OTC DRUG LABEL
Date: 20241231

ACTIVE INGREDIENTS: MENTHOL 10 g/100 mL; METHYL SALICYLATE 25 g/100 mL; CAPSAICIN 0.025 g/100 mL
INACTIVE INGREDIENTS: POLYSORBATE 20; POLYSORBATE 60; INDIAN FRANKINCENSE; STEARYL ALCOHOL; ALKYL (C12-15) BENZOATE; PROPYLPARABEN; CETOSTEARYL ALCOHOL; DIAZOLIDINYL UREA; WATER; PROPYLENE GLYCOL; GLYCERYL MONOSTEARATE; PEG-100 STEARATE; BORAGE SEED OIL; DIMETHYL SULFONE; ALOE VERA LEAF; CETYL ALCOHOL; STEARIC ACID; XANTHAN GUM; TROLAMINE; METHYLPARABEN; DMDM HYDANTOIN; LAVENDER OIL

New Terocin Lotion

ACTIVE INGREDIENT

Methyl Salicylate 25%
Capsaicin 0.025%
Menthol 10%

PURPOSE

Topical Analgesic

Uses

Temporarily relieves mild aches and pains of muscles or joints.

WARNINGS

Only for external use.

Do Not Use:

on open wounds, cuts, damaged or infected skin as well as in the eyes, mouth, genitals, or any other mucous membranes.

Consult your physician:

if pain is persistent or worsens or if using any other topical pain products.

Keep out of reach of children.

Consult physician for children under 12.

Consult physician for children under 12.

Directions

Wash and dry affected area. Shake bottle well before each use and gently rub over area of pain. Use is not recommended more than four times a day. Wash hands immediately afterwards to avoid contact with eyes.

DOSAGE AND ADMINISTRATION

As directed

INDICATIONS AND USAGE

Consult your physician

INACTIVE INGREDIENT

Aloe Barbadensis Leaf (Aloe Vera Gel) Juice, Aqua (Deionized Water), Borago Officinalis (Borage) Seed Oil, Boswellia Serrata Extract, C12-15 Alkyl Benzoate, Cetearyl Alcohol, Cetyl Alcohol, Diazolidinyl Urea, Dimethyl Sulfone (DMSO), DMDM Hydantoin, Glyceryl Stearate, Lavandula Angustifolia (Lavender) Oil, Methyl Paraben, PEG-100 Stearate, Polysorbate-20, Polysorbate-60, Propyl Paraben, Propylene Glycol, Stearic Acid, Stearyl Alcohol, Triethanolamine, Xanthan Gum.

HOW SUPPLIED

Bottle of:

120ml NDC: 80425-0256-01